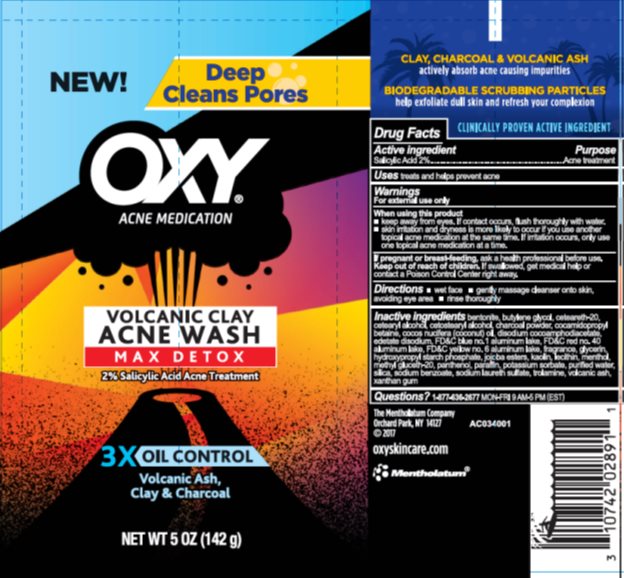 DRUG LABEL: OXY Volcanic Clay Acne Wash
NDC: 10742-8338 | Form: CREAM
Manufacturer: The Mentholatum Company
Category: otc | Type: HUMAN OTC DRUG LABEL
Date: 20241217

ACTIVE INGREDIENTS: SALICYLIC ACID 20 mg/1 g
INACTIVE INGREDIENTS: PANTHENOL; PARAFFIN; POTASSIUM SORBATE; WATER; SILICON DIOXIDE; SODIUM BENZOATE; SODIUM LAURETH-3 SULFATE; TROLAMINE; XANTHAN GUM; BENTONITE; BUTYLENE GLYCOL; POLYOXYL 20 CETOSTEARYL ETHER; CETOSTEARYL ALCOHOL; ACTIVATED CHARCOAL; COCAMIDOPROPYL BETAINE; COCONUT OIL; DISODIUM COCOAMPHODIACETATE; GLYCERIN; EDETATE DISODIUM; FD&C BLUE NO. 1; FD&C RED NO. 40; FD&C YELLOW NO. 6; HYDROGENATED JOJOBA OIL, RANDOMIZED; KAOLIN; LECITHIN, SOYBEAN; MENTHOL, UNSPECIFIED FORM; METHYL GLUCETH-20

Drug Facts - OXY Volcanic Clay Acne Wash

Active ingredient

Salicylic acid 2%

Purpose

Acne treatment

Uses

treats and helps prevent acne

Warnings

For external use only

When using this product

- keep away from eyes. If contact occurs, flush thoroughly with water.
- skin irritation and dryness is more likely to occur if you use another topical acne medication at the same time. If irritation occurs, only use one topical acne medication at a time.

If pregnant or breast-feeding,

ask a health professional before use

Keep out of reach of children.

If swallowed, get medical help or contact a Poison Control Center right away.

Directions

- wet face gently
- gently massage cleanser onto skin, avoiding eye area
- rinse thoroughly

Inactive ingredients

bentonite, butylene glycol, ceteareth-20, cetearyl alcohol, cetostearyl alcohol, charcoal powder, cocamidopropyl betaine, cocos nucifera (coconut) oil, disodium cocoamphodiacetate, edetate disodium, FD&C blue no. 1 aluminum lake, FD&C red no. 40 aluminum lake, FD&C yellow no. 6 aluminum lake, fragrance, glycerin, hydroxypropyl starch phosphate, jojoba esters, kaolin, lecithin, menthol, methyl gluceth-20, panthenol, paraffin, potassium sorbate, purified water, silica, sodium benzoate, sodium laureth sulfate, trolamine, volcanic ash, xanthan gum

Questions?

1-877-636-2677 MON-FRI 9 AM to 5 PM (EST)